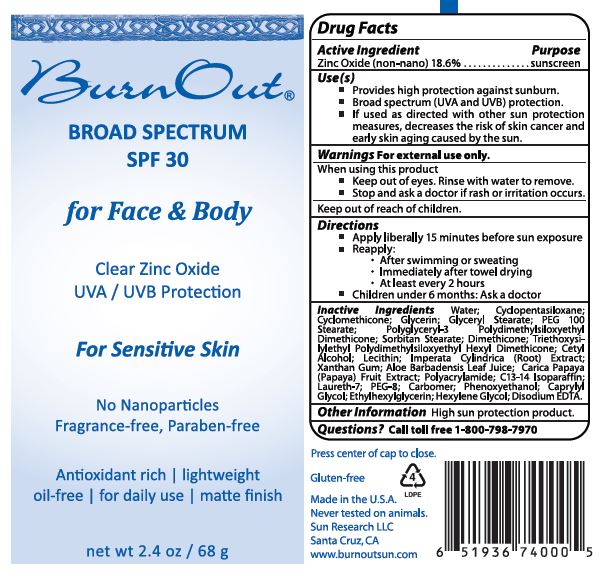 DRUG LABEL: Broad Spectrum SPF 30 for Face and Body
NDC: 62742-4116 | Form: CREAM
Manufacturer: Allure Labs Inc
Category: otc | Type: HUMAN OTC DRUG LABEL
Date: 20171204

ACTIVE INGREDIENTS: ZINC OXIDE 186 mg/1 g
INACTIVE INGREDIENTS: WATER; DIMETHICONE CROSSPOLYMER (450000 MPA.S AT 12% IN CYCLOPENTASILOXANE); CYCLOMETHICONE; GLYCERIN; GLYCERYL MONOSTEARATE; PEG-100 STEARATE; POLYGLYCERYL-3 POLYDIMETHYLSILOXYETHYL DIMETHICONE (4000 MPA.S); SORBITAN MONOSTEARATE; DIMETHICONE; CETYL ALCOHOL; LECITHIN, SOYBEAN; IMPERATA CYLINDRICA ROOT; POLYACRYLAMIDE (10000 MW); C13-14 ISOPARAFFIN; CARICA PAPAYA LEAF; ALOE VERA LEAF; PEG-8 CAPRYLIC/CAPRIC GLYCERIDES; CARBOMER COPOLYMER TYPE A (ALLYL PENTAERYTHRITOL CROSSLINKED); PHENOXYETHANOL; CAPRYLYL GLYCOL; ETHYLHEXYLGLYCERIN; HEXYLENE GLYCOL; LAURETH-7; XANTHAN GUM; EDETATE DISODIUM

Drug Facts

Active Ingredients: Zinc Oxide - 18.6%

Purpose: Sunscreen

Uses:

- Provided high protection against sunburn.
- Broad Spectrum (UVA and UVB) protection.
- If used with directed with other sun protection measures,decreases the risk of skin cancer and early skin aging caused by sun.

Warnings: For external use only.

When using this product keep out of eyes.Rinse with water to remove.

Stop use and ask a doctor if rash or irritation occurs.

Keep out of reach of children.

Directions:

- Apply generously 15 minutes before su exposure.
- Reapply at least every 2 hours. After swimming or sweating. Immediately after towel drying.
- Children under 6 months of age: ask a doctor.

Other Information High sun protection product.

QUESTIONS

Call toll free 1-800-798-7970

INACTIVE INGREDIENT

Water (Aqua), Cyclopentasiloxane, Glycerin, Glyceryl Stearate, PEG-100 Stearate, Polyglyceryl-3 Polydimethylsiloxyethyl Dimethicone, Sorbitan Stearate, Dimethicone, Triethoxysilylethyl Polydimethylsiloxyethyl Hexyl Dimethicone, Cetyl Alcohol, Polyacrylamide, C13-14 Isoparaffin, Lecithine, Imperata Cylindrica Root Extract, Xanthan Gum, Aloe Barbadensis Leaf Juice, Carica Papaya (Papaya) Fruit Extract, Phenoxyethanol, Caprylyl Glycol, Ethylhexylglycerin, Hexylene Glycol, Laureth-7, Carbomer, PEG-8, Disodium EDTA.

PACKAGE LABEL

Made in USA

Sun Research LLC

Santa Cruz, CA

www.burnoutsun.com